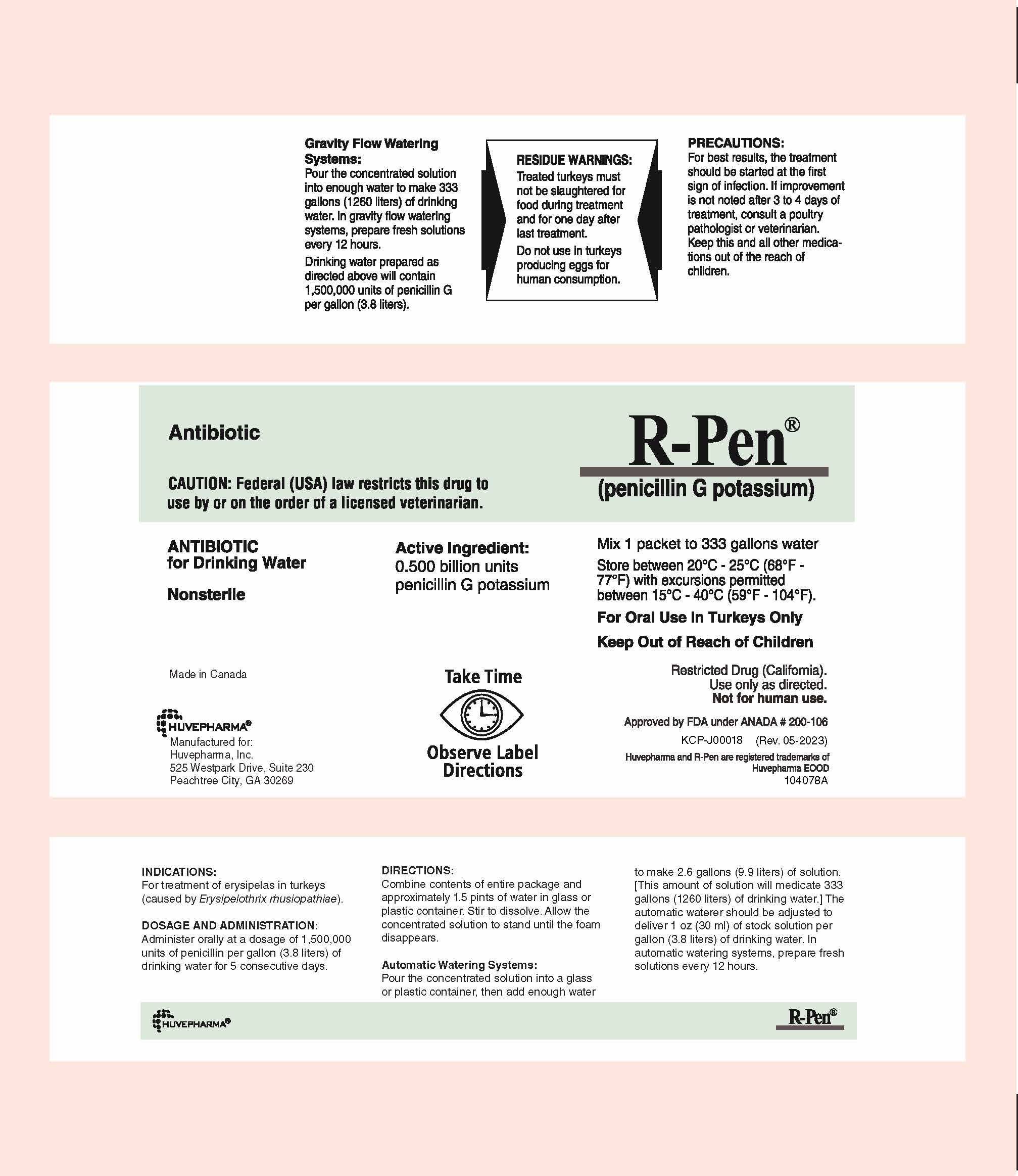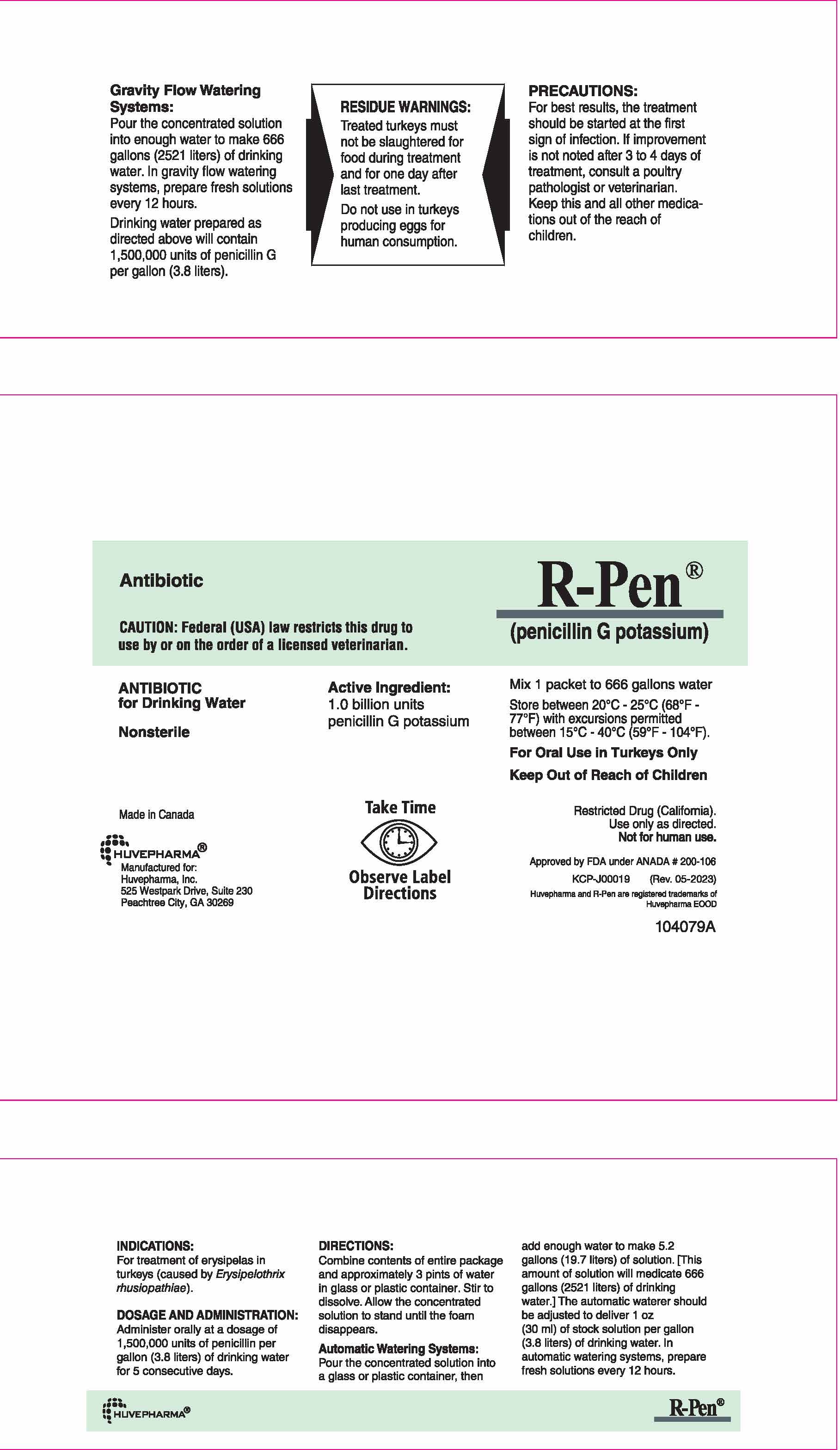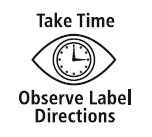 DRUG LABEL: R-PEN
NDC: 23243-6768 | Form: POWDER, FOR SOLUTION
Manufacturer: Huvepharma, Inc.
Category: animal | Type: PRESCRIPTION ANIMAL DRUG LABEL
Date: 20230707

ACTIVE INGREDIENTS: PENICILLIN G POTASSIUM 500000000 [iU]/500000000 [iU]

R-Pen®

0.5 BU Front Panel

Antibiotic

R-Pen®
(penicillin G potassium)

CAUTION: Federal (USA) law restricts this drug to use by or on the order of a licensed veterinarian.

ANTIBIOTIC
for Drinking Water

Nonsterile

Active Ingredient:
0.500 billion units
penicillin G potassium

Mix 1 packet to 333 gallons water

Store between 20°C - 25°C
(68°F - 77°F) with excursions
permitted between 15°C - 40°C
(59°F - 104°F).

For Oral Use in Turkeys Only

Keep Out of Reach of Children

Made in Canada

Huvepharma®
Manufactured for:
Huvepharma, Inc.
525 Westpark Dr, Suite 230
Peachtree City, GA 30269

Restricted Drug (California) -
Use only as directed.
Not for human use

Approved by FDA under ANADA # 200-106

KCP-J00018 (Rev. 05-2023)

Huvepharma and R-Pen are registered trademarks of Huvepharma EOOD

104078A

INSTRUCTIONS FOR USE

Gravity Flow Watering Systems:

Pour the concentrated solution into enough water to make 333 gallons (1260 liters) of drinking water. In gravity
flow watering systems, prepare fresh solutions every 12 hours.

Drinking water prepared as directed above will contain 1,500,000 units of penicillin G per gallon (3.8 liters).

RESIDUE WARNINGS:

Treated turkeys must not be slaughtered for food during treatment and for one day
after last treatment.
Do not use in turkeys producing eggs for human consumption.

PRECAUTIONS:

For best results, the treatment should be started at the first sign of infection. If improvement is not noted after 3 to 4 days of treatment, consult a poultry pathologist or veterinarian. Keep this and all other medications out of the reach of children.

INDICATIONS:

For treatment of erysipelas in turkeys (caused by Erysipelothrix rhusiopathiae).

DOSAGE AND ADMINISTRATION:

Administer orally at a dosage of 1,500,000 units of penicillin per gallon (3.8 liters) of drinking water for 5 consecutive days.

DIRECTIONS:
Combine contents of entire package and approximately 1.5 pints of water in glass or plastic container. Stir to dissolve. Allow the concentrated solution to stand until the foam disappears.

Automatic Watering Systems:
Pour the concentrated solution into a glass or plastic container, then add enough water to make 2.6 gallons (9.9 liters) of solution. [This amount of solution will medicate 333 gallons (1260 liters) of drinking water.] The automatic waterer should be adjusted to deliver 1 oz (30 ml) of stock solution per gallon (3.8 liters) of drinking water. In automatic watering systems, prepare fresh solutions every 12 hours.

1.0 BU Front Panel

Antibiotic

R-Pen®
(penicillin G potassium)

CAUTION: Federal (USA) law restricts this drug to use by or on the order of a licensed veterinarian.

ANTIBIOTIC for Drinking Water

Nonsterile

Active Ingredient:
1.0 billion units
penicillin G potassium

Mix 1 packet to 666 gallons water

Store between 20°C - 25°C
(68°F - 77°F) with excursions
permitted between 15°C - 40°C
(59°F - 104°F).

For Oral Use in Turkeys Only

Keep Out of Reach of Children

Made in Canada

Huvepharma

Manufactured for:
Huvepharma, Inc.
525 Westpark Dr, Suite 230
Peachtree City, GA 30269

Restricted Drug (California) -

Use only as directed.
Not for human use

Approved by FDA under ANADA # 200-106

KCP-J00019 (Rev. 05-2023)

Huvepharma and R-Pen are registered trademarks of Huvepharma EOOD

104079A

INSTRUCTIONS FOR USE

Gravity Flow Watering Systems:

Pour the concentrated solution into enough water to make 666 gallons (2521 liters) of
drinking water. In gravity flow watering systems, prepare fresh solutions every 12 hours.

Drinking water prepared as directed above will contain 1,500,000 units of penicillin G
per gallon (3.8 liters).

RESIDUE WARNINGS:

Treated turkeys must not be slaughtered for food during treatment and for one day after last treatment.
Do not use in turkeys producing eggs for human consumption.

PRECAUTIONS:

For best results, the treatment should be started at the first sign of infection. If improvement is not noted after 3 to 4 days of treatment, consult a poultry pathologist or veterinarian. Keep this and all other medications out of the reach of children.

INDICATIONS:

For treatment of erysipelas in turkeys (caused
by Erysipelothrix rhusiopathiae).

DOSAGE AND ADMINISTRATION:

Administer orally at a dosage of 1,500,000 units of penicillin per gallon (3.8 liters) of drinking water for 5 consecutive days.

DIRECTIONS:
Combine contents of entire package and approximately 3 pints of water in glass or plastic container. Stir to dissolve. Allow the concentrated solution to stand until the foam disappears.

Automatic Watering Systems:
Pour the concentrated solution into a glass or plastic container, then add enough water to make 5.2
gallons (19.7 liters) of solution. [This amount of solution will medicate 666 gallons (2521 liters) of drinking water.] The automatic waterer should be adjusted to deliver 1 oz (30 ml) of stock solution per gallon (3.8 liters) of drinking water. In automatic watering systems, prepare fresh solutions every 12 hours.